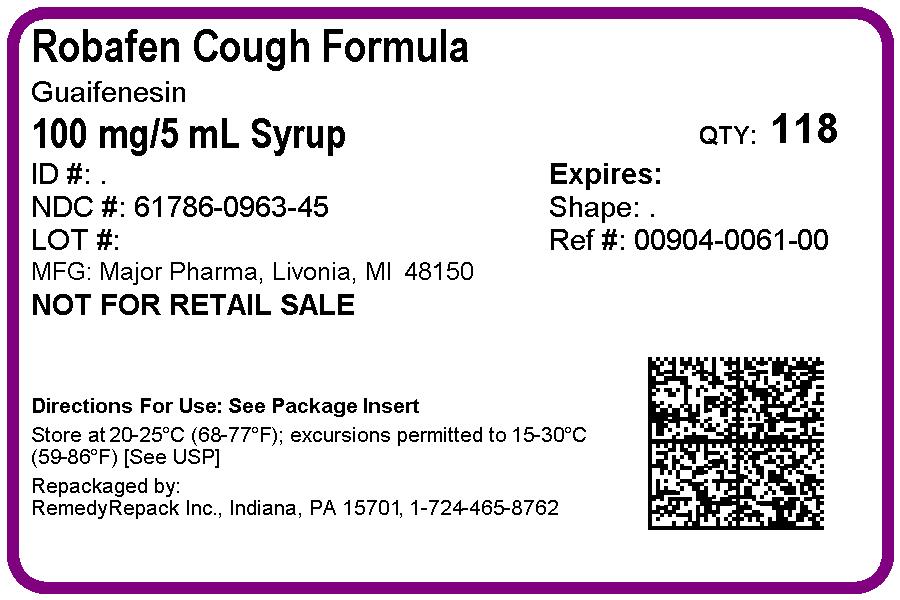 DRUG LABEL: ROBAFEN COUGH FORMULA
NDC: 61786-963 | Form: SYRUP
Manufacturer: REMEDYREPACK INC.
Category: otc | Type: HUMAN OTC DRUG LABEL
Date: 20171005

ACTIVE INGREDIENTS: GUAIFENESIN 100 mg/5 mL
INACTIVE INGREDIENTS: PROPYLENE GLYCOL; SODIUM BENZOATE; SACCHARIN SODIUM; ANHYDROUS CITRIC ACID; GLYCERIN; MENTHOL, UNSPECIFIED FORM; CORN SYRUP; WATER; CARAMEL; FD&C RED NO. 40

Robafen™ Syrup

Drug Facts

Active ingredient (in each 2 TSP (10 mL))

Guaifenesin USP 200 mg

Purpose

Expectorant

Uses

helps loosen phlegm (mucus) and thin bronchial secretions to make coughs more productive

Warnings

Ask a doctor before use if you have

- a persistent or chronic cough such as occurs with smoking, asthma, chronic bronchitis or emphysema
- a cough occurs with too much phlegm (mucus)

Stop use and ask a doctor if cough lasts more than 7 days, comes back, or is accompanied by fever, rash, or persistent headache. These could be signs of a serious condition.

PREGNANCY OR BREAST FEEDING

If pregnant or breast-feeding, ask a health professional before use.

KEEP OUT OF REACH OF CHILDREN

Keep out of the reach of children. In case of overdose, get medical help or contact a Poison Control Center right away.

Directions

- do not take more than 6 doses in any 24 hour period
- this product is not intended for use in children under 12 years of age
- TSP = teaspoonful

adults and children 12 years and over | 2 - 4 TSP every 4 hours
children under 12 years | do not use

Other information

- each TSP (5 mL) contains: sodium 3 mg
- store at 20°-25°C (68°-77°F). Do not refrigerate.

Inactive ingredients

caramel powder, citric acid, corn syrup, FD&C Red #40, glycerin, menthol, propylene glycol, purified water, saccharin sodium, sodium benzoate

Questions or comments?

(800) 616-2471

Distributed by
MAJOR® PHARMACEUTICALS
17177 N Laurel Park Drive, Suite 233,
Livonia, MI 48152

PACKAGE LABEL

DRUG: ROBAFEN COUGH FORMULA

GENERIC: Guaifenesin

DOSAGE: SYRUP

ADMINSTRATION: ORAL

NDC: 61786-963-45

COLOR: brown

FLAVOR: MENTHOL

PACKAGING: 118 mL in 1 BOTTLE

ACTIVE INGREDIENT(S):

- Guaifenesin 100mg in 5mL

INACTIVE INGREDIENT(S):

- Corn Syrup
- FD&C Red no. 40
- Menthol, Unspecified Form
- Caramel
- Water
- Glycerin
- Sodium Benzoate
- Propylene Glycol
- Anhydrous Citric Acid
- Saccharin Sodium